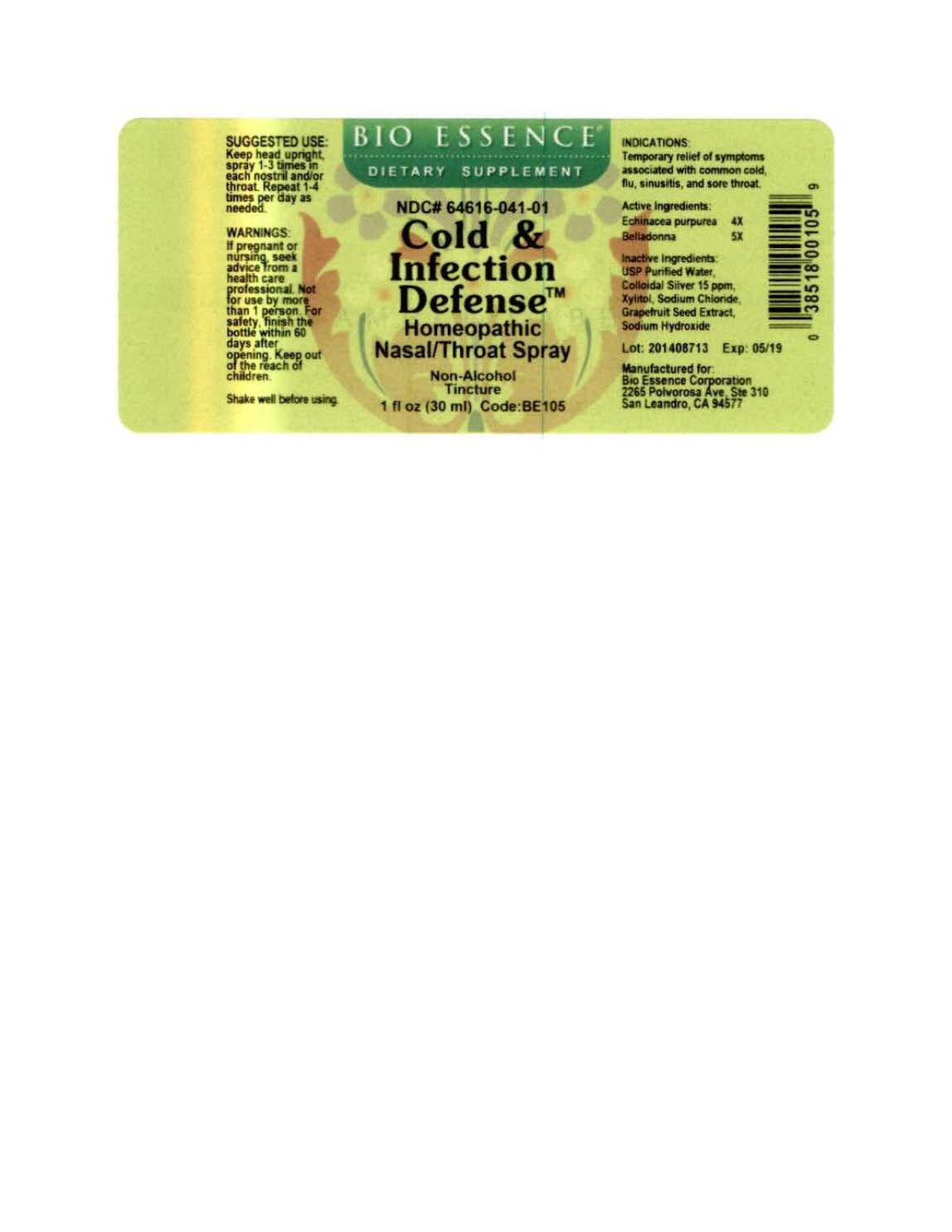 DRUG LABEL: Cold and Infection Defense
NDC: 64616-041 | Form: LIQUID
Manufacturer: Vitality Works, Inc
Category: homeopathic | Type: HUMAN OTC DRUG LABEL
Date: 20221230

ACTIVE INGREDIENTS: ECHINACEA PURPUREA 4 [hp_X]/1 mL; ECHINACEA PURPUREA ROOT 4 [hp_X]/1 mL; BELLADONNA LEAF 5 [hp_X]/1 mL
INACTIVE INGREDIENTS: WATER; SILVER; XYLITOL; SODIUM CHLORIDE; CITRUS PARADISI SEED; SODIUM HYDROXIDE

Cold and Infection Defense

Cold and Infection Defense

Echinacea purpurea 4X

Belladonna 5X

Cold and Infection Defense

USP Purified Water, Collodial Silver 15 ppm, Xylitol, Sodium Chloride, Grapefruit Seed Extract, Sodium Hydroxide

Cold and Infection Defense

If pregnant or nursing, seek advice from a health care professional. Not for use by more that 1 person. For safety finish the bottle within 60 days after opening. Keep out of reach of children.

Cold and Infection Defense

Keep out of reach of children.

Cold and Infection Defense

Temporary relief of symptoms associated with common cold, flu, sinusitis and sore throat.

Cold and Infection Defense

Kee head upright, spray 1-3 times in each nostril and/or throat. Repeat 1-4 times per day as needed.

Cold and Infection Defense

Temporary relief of syptoms associated with common cold, flu, sinusitis, and sore throat.